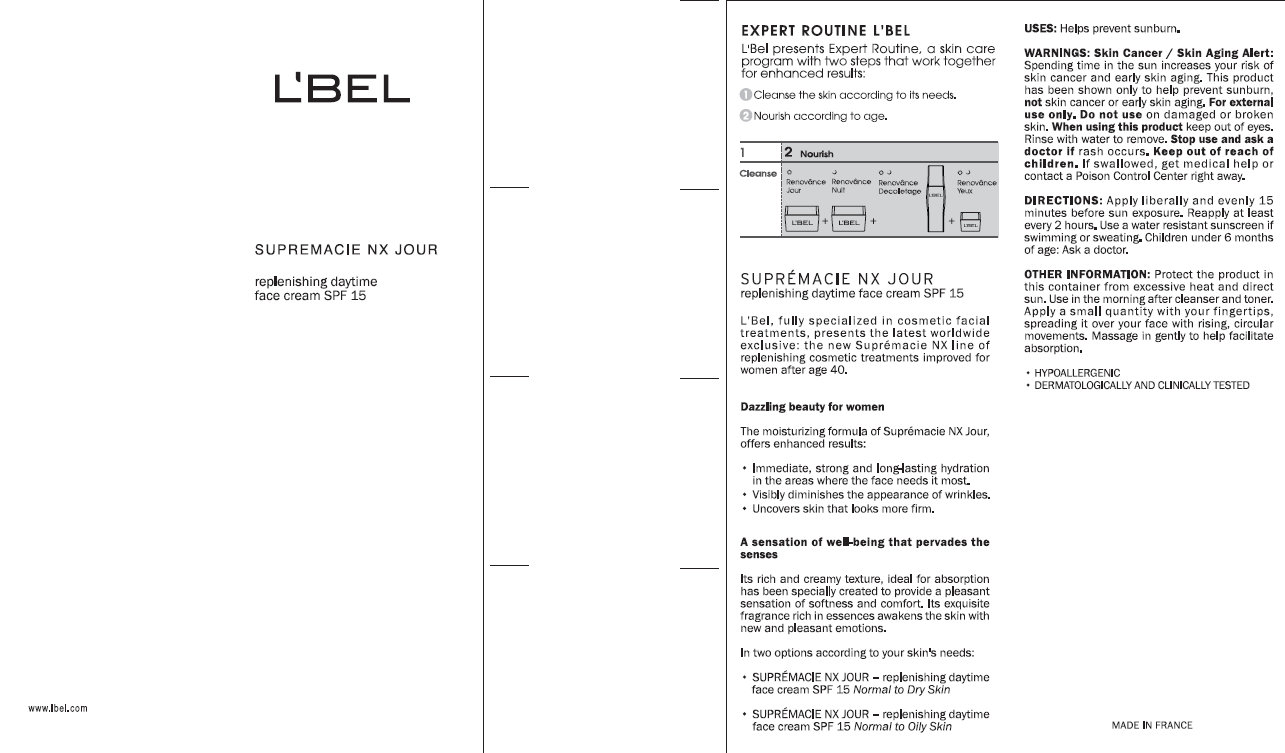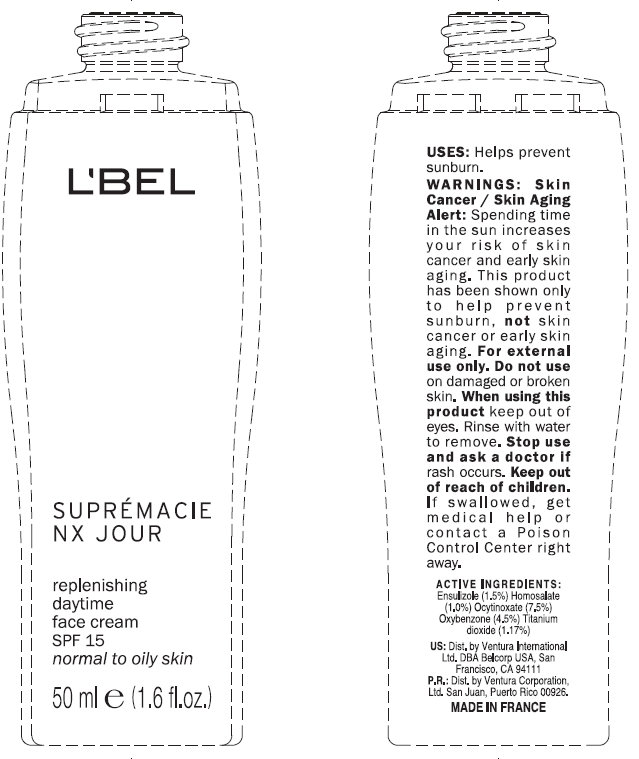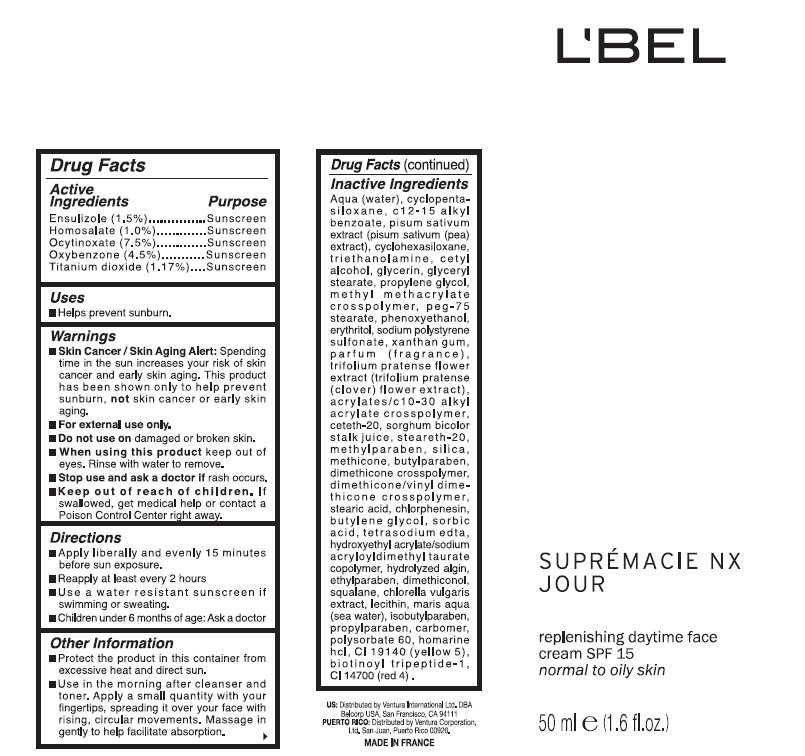 DRUG LABEL: LBEL SUPREMACIE NX JOUR Replenishing Daytime Face SPF 15 Normal To Oily Skin
NDC: 43596-0006 | Form: CREAM
Manufacturer: Ventura Corporation, LTD
Category: otc | Type: HUMAN OTC DRUG LABEL
Date: 20120328

ACTIVE INGREDIENTS: ENSULIZOLE 1.5 mL/100 mL; HOMOSALATE 1 mL/100 mL; OCTINOXATE 7.5 mL/100 mL; OXYBENZONE 4.5 mL/100 mL; TITANIUM DIOXIDE 1.17 mL/100 mL
INACTIVE INGREDIENTS: WATER; CYCLOMETHICONE 5; ALKYL (C12-15) BENZOATE; PEA; CYCLOMETHICONE 6; TROLAMINE; CETYL ALCOHOL; GLYCERIN; GLYCERYL MONOSTEARATE; PROPYLENE GLYCOL; PEG-75 STEARATE; PHENOXYETHANOL; ERYTHRITOL; SODIUM POLYSTYRENE SULFONATE; XANTHAN GUM; TRIFOLIUM PRATENSE FLOWER; CARBOMER INTERPOLYMER TYPE A (55000 MPA.S); CETETH-20; SORGHUM BICOLOR STEM JUICE; STEARETH-20; METHYLPARABEN; SILICON DIOXIDE; BUTYLPARABEN; DIMETHICONE; STEARIC ACID; CHLORPHENESIN; BUTYLENE GLYCOL; SORBIC ACID; EDETATE SODIUM; ETHYLPARABEN; SQUALANE; CHLORELLA VULGARIS; ISOBUTYLPARABEN; PROPYLPARABEN; POLYSORBATE 60; FD&C YELLOW NO. 5; BIOTINOYL TRIPEPTIDE-1; FD&C RED NO. 4

L'BEL SUPREMACIE NX JOUR Replenishing Treatment Daytime Face Cream SPF 15 Normal To Oily Skin

Active Ingredients

ENSULIZOLE (1.50%)
HOMOSALATE (1.00%)
OCTINOXATE (7.50%)
OXYBENZONE (4.50%)
TITANIUM DIOXIDE (1.17%)

Uses

- Helps prevent sunburn.

Warnings

- Skin Cancer / Skin Aging Alert: Spending time in the sun increases your risk of skin cancer and early skin aging. This product has been shown only to help prevent sunburn, not skin cancer or early skin aging.
- For external use only.

Do not use on

damaged or broken skin.

When using this product

keep out of eyes. Rinse with water to remove.

Stop use and ask a doctor if

rash occurs.

Keep out of reach of children.

If swallowed, get medical help or contact a Poison Control Center right away.

Directions

- Apply liberally and evenly 15 minutes before sun exposure.
- Reapply at least every 2 years
- Use a water resistant sunscreen if swimming or sweating.
- Children under 6 months of age: Ask a doctor.

Other Information

- Protect the product in this container from excessive heat and direct sun.
- Use in the morning after cleanser and toner. Apply a small quantity with your fingertips, spreading it over your face with rising, circular movements. Message in gently to help facilitate absorption.

Inactive Ingredients

Aqua (water), cyclopentasiloxane, c12-15 alkyl benzoate, pisum sativum extract (pisum sativum (pea) extract), cyclohexasiloxane, triethanolamine, cetyl alcohol, glycerin, glyceryl stearate, propylene glycol, methyl methacrylate crosspolymer, peg-75 stearate, phenoxyethanol, erythritol, sodium polystyrene sulfonate, xanthan gum, parfum (fragrance), trifolium pratense flower extract (trifolium pratense (clover) flower extract), acrylates/c10-30 alkyl acrylate crosspolymer, ceteth-20, sorghum bicolor stalk juice, steareth-20, methylparaben, silica, methicone, butylparaben, dimethicone crosspolymer, dimethicone/vinyl dimethicone crosspolymer, stearic acid, chlorphenesin, butylene glycol, sorbic acid, tetrasodium edta, hydroxyethyl acrylate/sodium acryloyldimethyl taurate copolymer, hydrolyzed algin, ethylparaben, dimethiconol, squalane, chlorella vulgaris extract, lecithin, maris aqua (sea water), isobutylparaben, propylparaben, carbomer, polysorbate 60, homarine hcl, ci 19140 (yellow 5), biotinoyl tripeptide-1, ci 14700 (red 4).

Purpose

Sunscreen

EXPERT ROUTINE L'BEL

L'Bel presents Expert Routine, a skin care program with two steps that work together for enhanced results:
1. Cleanse the skin according to its needs
2. Nourish according to the age.

SUPREMACIE NX JOUR
replenishing daytime face cream SPF 15

L'Bel, fully specialized in cosmetic facial treatment, presents the latest worldwide exclusive: the new Supremacie NX line of replenishing cosmetic treatments improved for women after age 40.

Dazzling beauty for women

The moisturizing formula of Supremacie NX Jour, Offers enhanced results:

- Immediate, strong and long-lasting hydration in the areas where the face needs it most.
- Visibly diminishes the appearance of wrinkles.
- Uncovers skin that looks more firm.

A sensation of well-being that pervades the senses

Its rich and creamy texture, ideal for absorption has been specially created to provide a pleasant sensation of softness and comfort. Its exquisite fragrance rich in essences awakens the skin with new and pleasant emotions.

In two options according to your skin's needs:

- SUPREMACIE NX JOUR - replenishing daytime face cream SPF 15 Normal to Dry Skin

- SUPREMACIE NX JOUR - replenishing daytime face cream SPF 15 Normal to Oily Skin

USES: Helps prevent sunburn.

WARNINGS: Skin Cancer / Skin Aging Alert: Spending time in the sun increases your risk of skin cancer and early skin aging. This product has been shown only to help prevent sunburn, not skin cancer or early skin aging. For external use only. Do not use on damaged or broken skin. When using this product keep out of eyes. Rinse with water to remove. Stop use and ask a doctor if rash occurs. Keep out of reach of children. If swallowed, get medical help or contact a Poison Control Center right away.
Directions: Apply liberally and evenly 15 minutes before sun exposure. Reapply at least every 2 hours.Use a water resistant sunscreen if swimming or sweating. Children under 6 months of age: Ask a doctor.
Other information: Protect the product in this container from excessive heat and direct sun. Use in the morning after cleanser and toner. Apply a small quantity with your fingertips, spreading it over your face with rising, circular movements. Message in gently to help facilitate absorption.

- HYPOALLERGENIC
- DERMATOLOGICALLY AND CLINICALLY TESTED

PACKAGE LABEL

L'BEL

SUPREMACIE NX JOUR
replenishing daytime face cream SPF 15
normal to oily skin
50 ml e (1.6 fl.oz.)
US: Dist. by Ventura International Ltd. DBA Belcorp USA, San Francisco, CA 94111
P.R.: Dist. by Ventura Corporation Ltd. San Juan, Puerto Rico 00926 MADE IN FRANCE